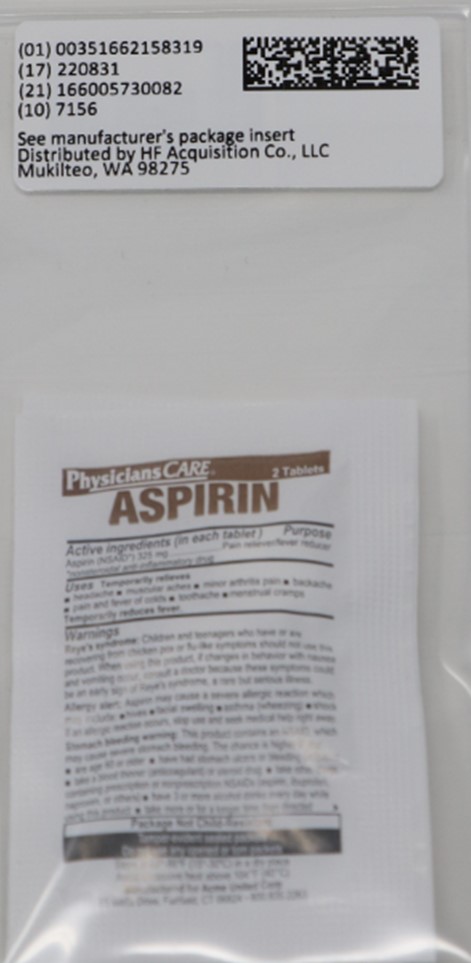 DRUG LABEL: ASPIRN
NDC: 51662-1583 | Form: TABLET, FILM COATED
Manufacturer: HF Acquisition Co LLC, DBA HealthFirst
Category: otc | Type: HUMAN OTC DRUG LABEL
Date: 20240904

ACTIVE INGREDIENTS: ASPIRIN 325 mg/1 1
INACTIVE INGREDIENTS: CROSCARMELLOSE SODIUM; MINERAL OIL; TITANIUM DIOXIDE; CELLULOSE, MICROCRYSTALLINE; HYPROMELLOSES; STARCH, CORN

DRUG FACTS

Active ingredient (in each tablet)

Aspirin (NSAID*) 325 mg

*nonsteroidal anti-inflammatory drug

PURPOSE

Pain reliever/fever reducer

USES

Temporarily relieves minor aches and pains associated with

■ headache

■ minor arthritis pain

■ common cold

■ menstrual cramps

■ muscular aches

■ backache

■ toothache

Temporarily reduces fever.

WARNINGS

Reye's syndrome: Children and teenagers who have or are recovering from chicken pox or flu-like symptoms should not use this product. When using this product, if changes in behavior with nausea and vomiting occur, consult a doctor because these symptoms could be an early sign of Reye's syndrome, a rare but serious illness.

Allergy alert: Aspirin may cause a severe allergic reaction which may include:

■ hives

■ skin reddening

■ facial swelling

■ rash

■ asthma (wheezing)

■ blisters

■ shock

If an allergic reaction occurs, stop use and seek medical help right away.

Stomach bleeding warning: This product contains an NSAID, which may cause severe stomach bleeding. The chance is higher if you:

■ are age 60 or older

■ have had stomach ulcers or bleeding problems

■ take a blood thinning (anticoagulant) or steroid drug

■ take other drugs containing prescription or nonprescription NSAIDs (aspirin, ibuprofen, naproxen, or others)

■ have 3 or more alcohol drinks every day while using this product

■ take more or for a longer time than directed

DO NOT USE

■ if you have ever had an allergic reaction to any other pain reliever/ fever reducer

■ right before or after heart surgery

■ if you are taking prescription drugs for gout, diabetes or arthritis

ASK DOCTOR

■ stomach bleeding warning applies to you

■ you have a history of stomach problems such as heartburn

■ you have high blood pressure, heart disease, liver cirrhosis, or kidney disease

■ you are taking a diuretic

■ you have asthma

ASK DOCTOR/PHARMACIST

■ under a doctor's care for any serious condition

■ taking any other drug

WHEN USING

take with food or milk if stomach upset occurs

STOP USE

■ you experience any of the following signs of stomach bleeding:

■ feel faint

■ vomit blood

■ have bloody or black stools

■ have stomach pain that does not get better

■ pain gets worse or lasts more than 10 days

■ fever gets worse or lasts more than 3 days

■ you have difficulty swallowing

■ if ringing in the ears or loss of hearing occurs

■ redness or swelling is present in the painful area

■ any new symptoms appear

PREGNANCY OR BREAST FEEDING

ask a health professional before use. It is especially important not to use aspirin during the last 3 months of pregnancy unless definitely directed to do so by a doctor because it may cause problems in the unborn child or complications during delivery.

KEEP OUT OF REACH OF CHILDREN

In case of overdose, get medical help or contact a Poison Control Center right away.

DOSAGE AND ADMINISTRATION

do not take more than directed

■ the smallest effective dose should be used

■ do not take longer than 10 days, unless directed by a doctor (see Warnings)

■ drink a full glass of water with each dose

Adults and children: Take 1 or 2 tablets with water every 4 hours as needed. Do not
(12 years and older) take more than 12 tablets in 24 hours, or as directed by a doctor.

Children under 12 years: Do not give to children under 12 years of age.

INACTIVE INGREDIENT

corn starch, croscarmellose sodium, hypromellose, microcrystalline cellulose, mineral oil, titanium dioxide

INDICATIONS AND USAGE

do not take more than directed

■ the smallest effective dose should be used

■ do not take longer than 10 days, unless directed by a doctor (see Warnings)

■ drink a full glass of water with each dose

Adults and children: Take 1 or 2 tablets with water every 4 hours as needed. Do not
(12 years and older) take more than 12 tablets in 24 hours, or as directed by a doctor.

Children under 12 years: Do not give to children under 12 years of age.

HOW SUPPLIED

1 (2 Pack) 325 NSAID